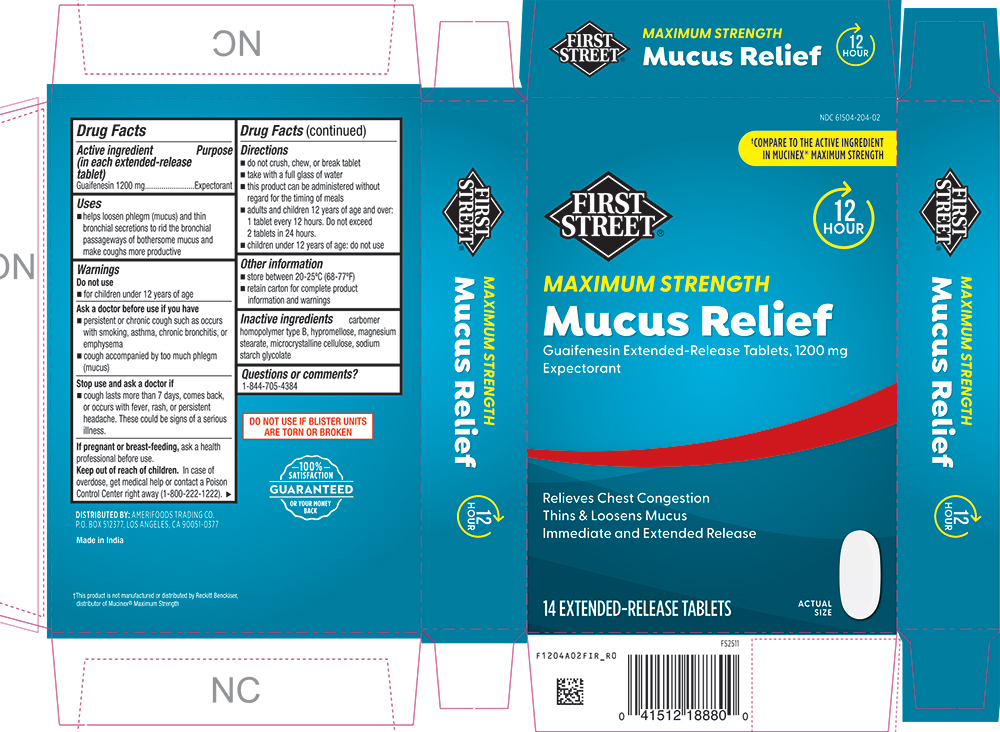 DRUG LABEL: Mucus Relief
NDC: 61504-204 | Form: TABLET, EXTENDED RELEASE
Manufacturer: AMERIFOODS TRADING COMPANY
Category: otc | Type: HUMAN OTC DRUG LABEL
Date: 20251120

ACTIVE INGREDIENTS: GUAIFENESIN 1200 mg/1 1
INACTIVE INGREDIENTS: CARBOMER HOMOPOLYMER TYPE B (ALLYL SUCROSE CROSSLINKED); HYPROMELLOSE 2910 (15 MPA.S); SODIUM STARCH GLYCOLATE TYPE A; MAGNESIUM STEARATE; MICROCRYSTALLINE CELLULOSE

1204-FIR-2025-1120

Drug Facts

Active ingredient (in each extended-release tablet)

Guaifenesin 1200 mg

Purpose

Expectorant

Uses

■ helps loosen phlegm (mucus) and thin bronchial secretions to rid the bronchial passageways of bothersome mucus and make coughs more productive

Warnings

Do not use

■ for children under 12 years of age

Ask a doctor before use if you have

■ persistent or chronic cough such as occurs with smoking, asthma, chronic bronchitis, or emphysema

■ cough accompanied by too much phlegm (mucus)

Stop use and ask a doctor if

■ cough lasts more than 7 days, comes back, or occurs with fever, rash, or persistent headache. These could be signs of a serious illness.

PREGNANCY OR BREAST FEEDING

If pregnant or breast-feeding, ask a health professional before use.

Keep out of reach of children.In case of overdose, get medical help or contact a Poison Control Center right away (1-800-222-1222).

Directions

■ do not crush, chew, or break tablet

■ take with a full glass of water

■ this product can be administered without regard for the timing of meals

■ adults and children 12 years of age and over: 1 tablet every 12 hours. Do not exceed 2 tablets in 24 hours.

■ children under 12 years of age: do not use

Other information

■ store between 20-25ºC (68-77ºF)

■ retain carton for complete product information and warnings

Inactive ingredients

carbomer homopolymer type B, hypromellose, magnesium stearate, microcrystalline cellulose, sodium starch glycolate

Questions or comments?

1-844-705-4384

PRINCIPAL DISPLAY PANEL

NDC 61504-204-02

†COMPARE TO THE ACTIVE INGREDIENT IN MUCINEX® MAXIMUM STRENGTH

FIRST STREET®

12 HOUR

MAXIMUM STRENGTH

Mucus Relief

Guaifenesin Extended-Release Tablets, 1200 mg

Expectorant

Relieves Chest Congestion

Thins & Loosens Mucus

Immediate & Extended Release

14 EXTENDED-RELEASE TABLETS

ACTUAL SIZE